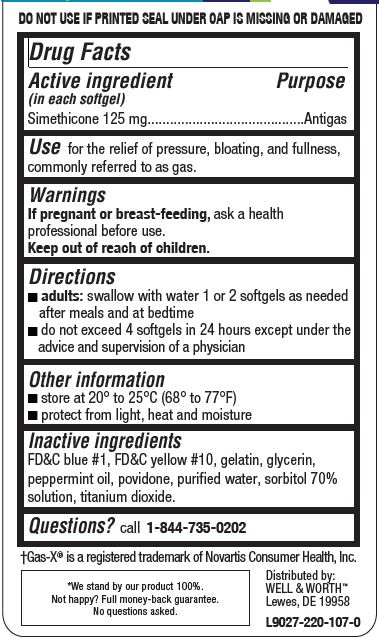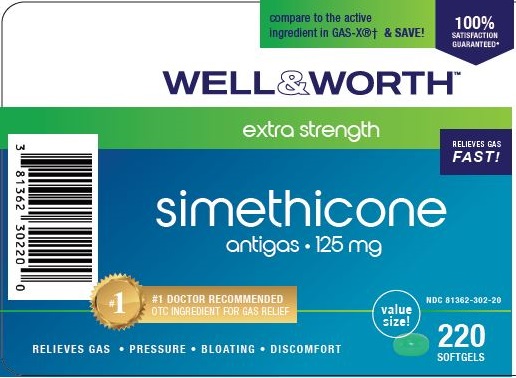 DRUG LABEL: EXTRA STRENGTH SIMETHICONE ANTIGAS
NDC: 81362-302 | Form: CAPSULE, GELATIN COATED
Manufacturer: LLS HEALTH LLC
Category: otc | Type: HUMAN OTC DRUG LABEL
Date: 20240103

ACTIVE INGREDIENTS: DIMETHICONE 125 mg/1 1
INACTIVE INGREDIENTS: FD&C BLUE NO. 1; D&C YELLOW NO. 10; GELATIN; GLYCERIN; PEPPERMINT OIL; POVIDONE; WATER; SORBITOL SOLUTION 70%; TITANIUM DIOXIDE

LLS HEALTH - WELL & WORTH EXTRA STRENGTH SIMETHICONE ANTIGAS 125 MG

Active ingredient (in each softgel)

Simethicone 125 mg

Purpose

Antigas

Use

for the relief of pressure, bloating, and fullness, commonly referred to as gas.

Warnings

If pregnant or breast-feeding, ask a health professional before use.

Keep out of reach of children.

Directions

- adults: swallow with water 1 or 2 softgels as needed after meals and at bedtime
- do not exceed 4 softgels in 24 hours except under the advice and supervision of a physician

Other information

- store at 20° to 25°C (68° to 77°F)
- protect from light, heat and moisture

Inactive ingredients

FD&C blue #1, FD&C yellow #10, gelatin, glycerin, peppermint oil, povidone, purified water, sorbitol 70% solution, titanium dioxide.

Questions?

call 1-844-735-0202